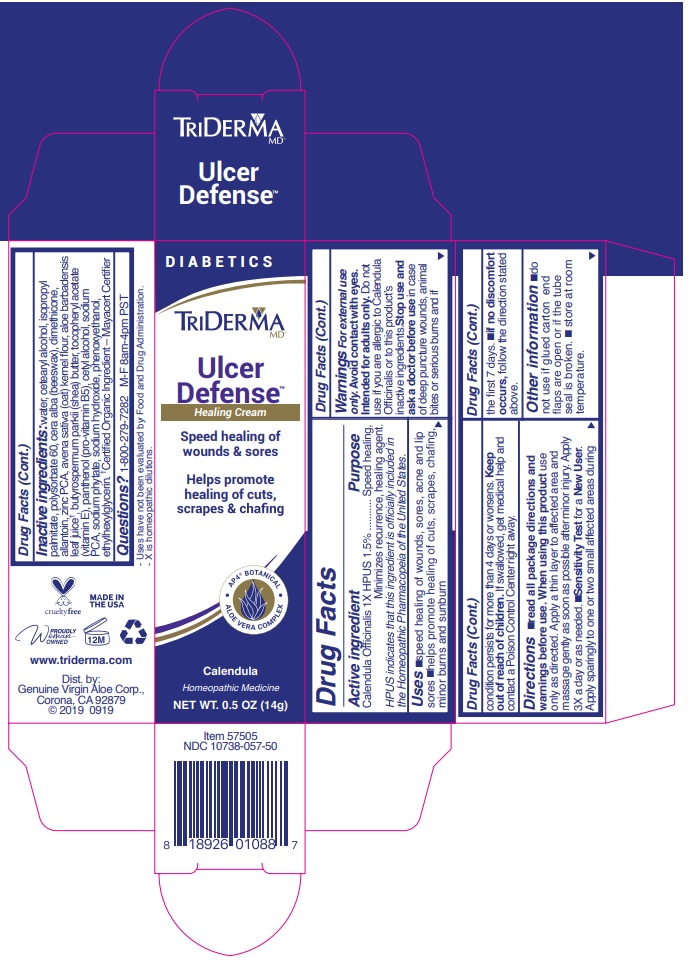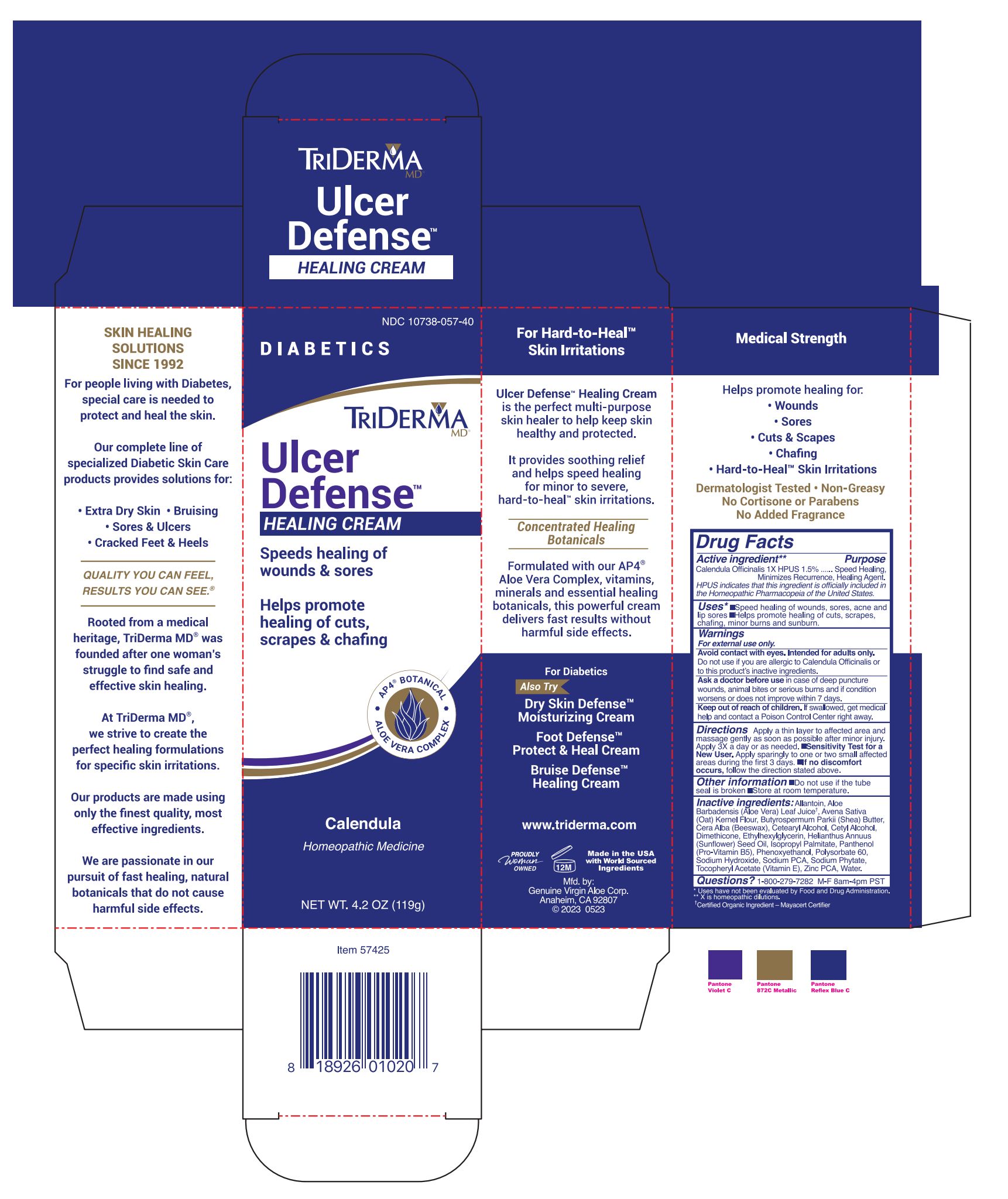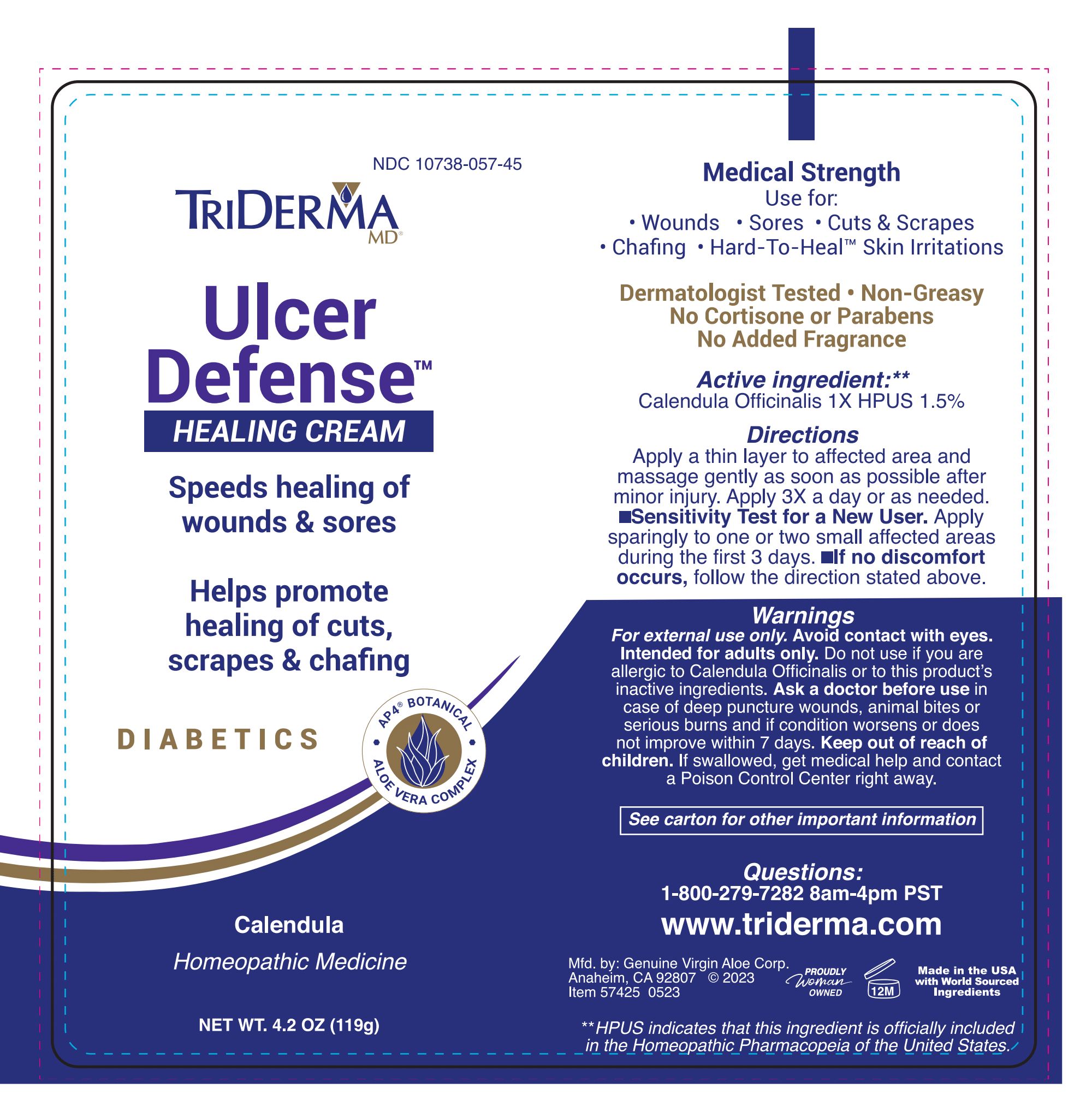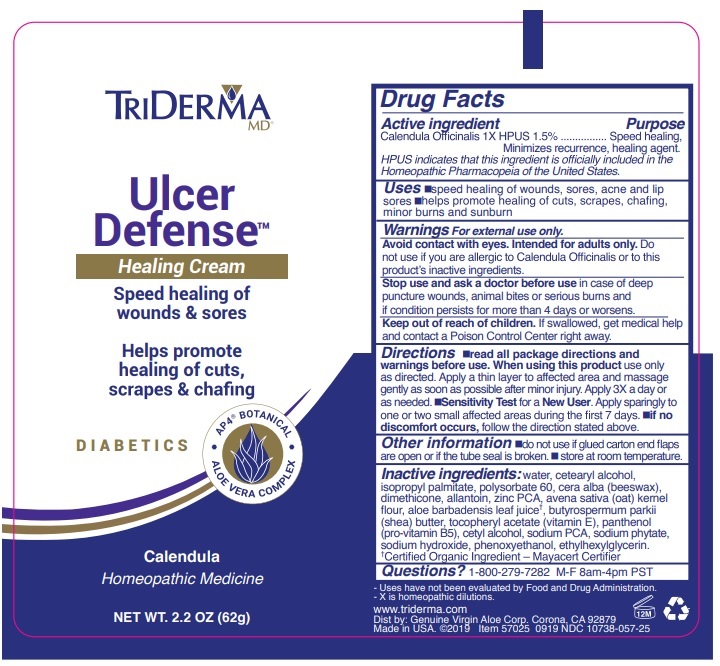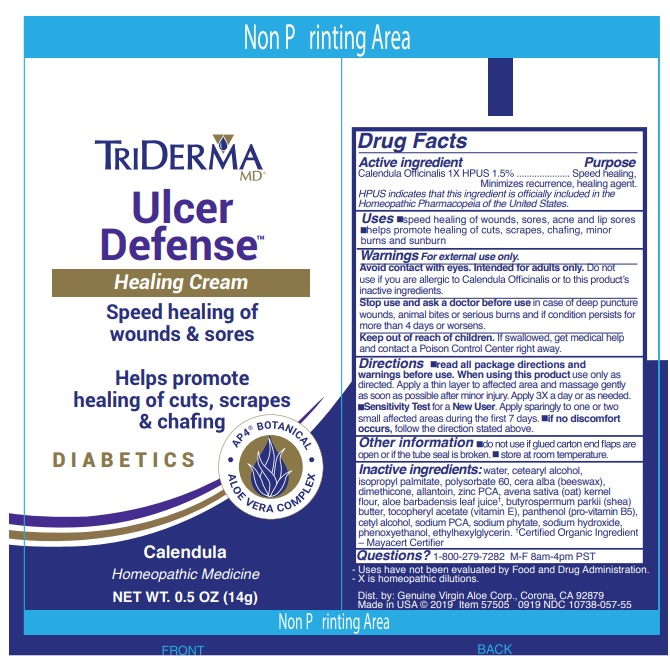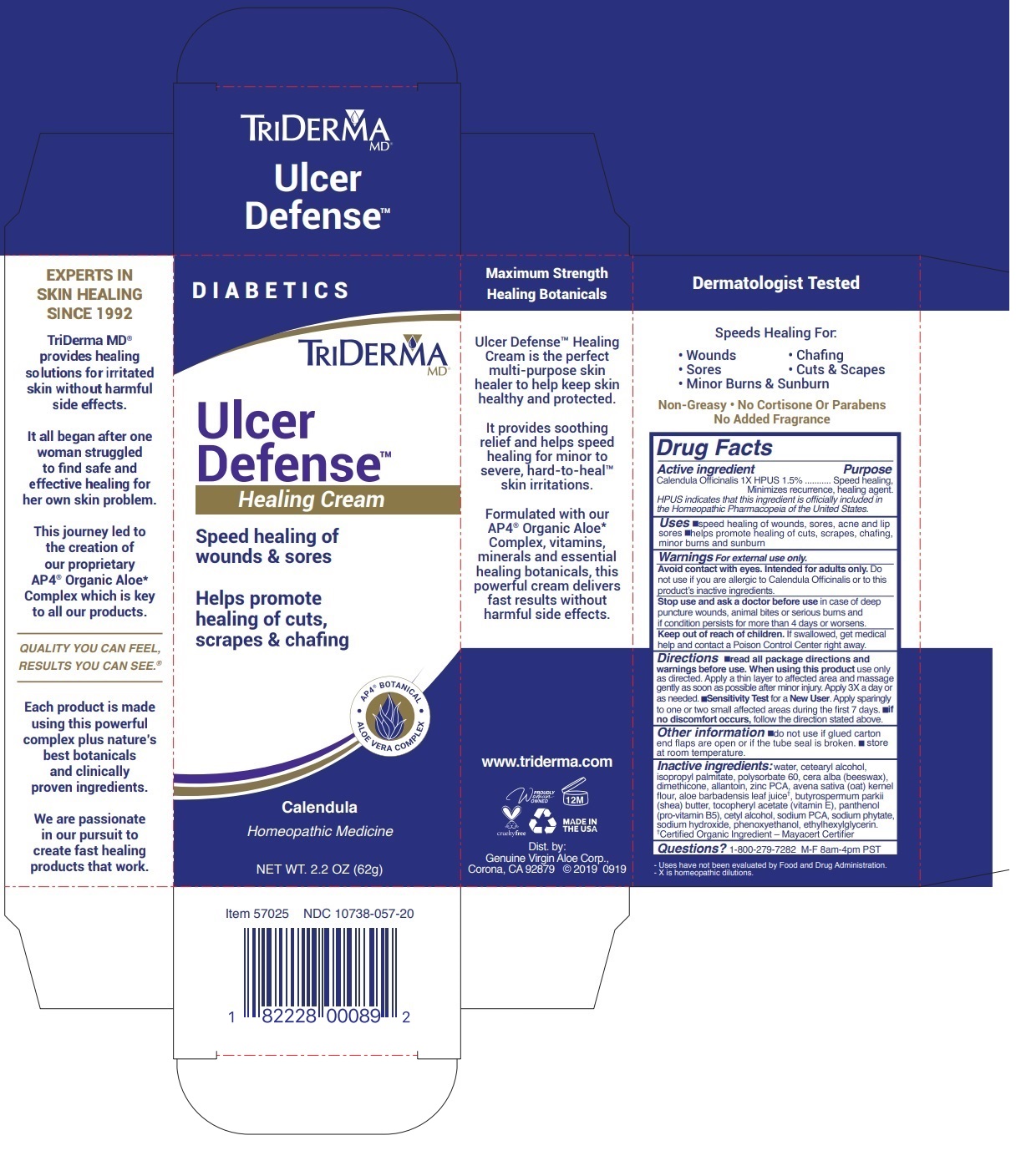 DRUG LABEL: TRIDERMA ULCER DEFENSE HEALING
NDC: 10738-057 | Form: CREAM
Manufacturer: Genuine Virgin Aloe Corporation
Category: homeopathic | Type: HUMAN OTC DRUG LABEL
Date: 20260124

ACTIVE INGREDIENTS: CALENDULA OFFICINALIS FLOWERING TOP 1.5 g/100 g
INACTIVE INGREDIENTS: CETOSTEARYL ALCOHOL; WATER; ISOPROPYL PALMITATE; POLYSORBATE 60; YELLOW WAX; DIMETHICONE; ALLANTOIN; ZINC PIDOLATE; OATMEAL; ALOE VERA LEAF; SHEA BUTTER; .ALPHA.-TOCOPHEROL ACETATE; PANTHENOL; CETYL ALCOHOL; SODIUM PYRROLIDONE CARBOXYLATE; PHYTATE SODIUM; SODIUM HYDROXIDE; PHENOXYETHANOL; ETHYLHEXYLGLYCERIN

TRIDERMA Ulcer Defense Healing Cream

Active ingredient

Calendula Officinalis 1X HPUS 1.5%

Purpose

Speed healing, Minimizes recurrence, healing agent.

HPUS indicates that this ingredient is officially included in the Homeopathic Pharmacopeia of the United States.

INDICATIONS AND USAGE

Uses •speed healing of wounds, sores, acne and lip sores •helps promote healing of cuts, scrapes, chafing, minor burns and sunburn

Warnings For external use only.

Avoid contact with eyes. Intended for adults only. Do not use if you are allergic to Calendula Officinalis or to this product's inactive ingredients.

Stop use and ask a doctor before use in case of deep puncture wounds, animal bites or serious burns and if condition persists for more than 4 days or worsens.

Keep out of reach of children. If swallowed, get medical help and contact a Poison Control Center right away.

DOSAGE AND ADMINISTRATION

Directions •read all package directions and warnings before use. When using this product use only as directed. Apply a thin layer to affected area and massage gently as soon as possible after minor injury. Apply 3X a day or as needed. •Sensitivity Test for a New User. Apply sparingly to one or two small affected areas during the first 7 days. •if no discomfort occurs, follow the direction stated above.

Other information •do not use if glued carton end flaps are open or if the tube seal is broken. • store at room temperature.

Inactive ingredients:

Aloe Barbadensis Leaf Juice†

Avena Sativa (Oat) Kernel Flour

Beeswax

Butyrospermum Parkii (Shea) Butter

Calendula Officinalis Flower Extract

Cetearyl Alcohol

Cetyl Alcohol

Dimethicone

Ethylhexylglycerin

Helianthus Annuus (Sunflower) Seed Oil

Isopropyl Palmitate

Olea Europaea (Olive) Fruit Oil

Panthenol

Phenoxyethanol

Polysorbate 60

Sodium Hydroxide

Sodium PCA

Sodium Phytate

Tocopheryl Acetate

Water (Aqua)

Zinc PCA

†Certified Organic Ingredient — Mayacert Certifier

QUESTIONS

Questions? 1-800-279-7282 M-F 8am-4pm PST

Speed healing of wounds & sores

Helps promote healing of cuts, scrapes & chafing

DIABETICS

AP4® Botanical

ALOE VERA COMPLEX

Calendula

Homeopathic Medicine

Maximum Strength

Healing Botanicals

Ulcer Defense™ Healing Cream is the perfect multi-purpose skin healer to help keep skin healthy and protected.

It provides soothing relief and helps speed healing for minor to severe, hard-to-heal™ skin irritations.

Formulated with our AP4® Organic Aloe* Complex, vitamins, minerals and essential healing botanicals, this powerful cream delivers fast results without harmful side effects.

www.triderma.com

MADE IN THE USA

Mfd. by: Genuine Virgin Aloe Corp., Anaheim, CA 92807

Dermatologist Tested

Speeds Healing For:

• Minor Burns & Sunburn

Non-Greasy • No Cortisone Or Parabens

No Added Fragrance

- Uses have not been evaluated by Food and Drug Administration.

- X is homeopathic dilutions.

EXPERTS IN SKIN HEALING SINCE 1992

TriDerma MD® provides healing solutions for irritated skin without harmful side effects.

It all began after one woman struggled to find safe and effective healing for her own skin problem.

This journey led to the creation of our proprietary AP4® Organic Aloe* Complex which is key to all our products.

QUALITY YOU CAN FEEL, RESULTS YOU CAN SEE.®

Each product is made using this powerful complex plus nature’s best botanicals and clinically proven ingredients.

We are passionate in our pursuit to create fast healing products that work.